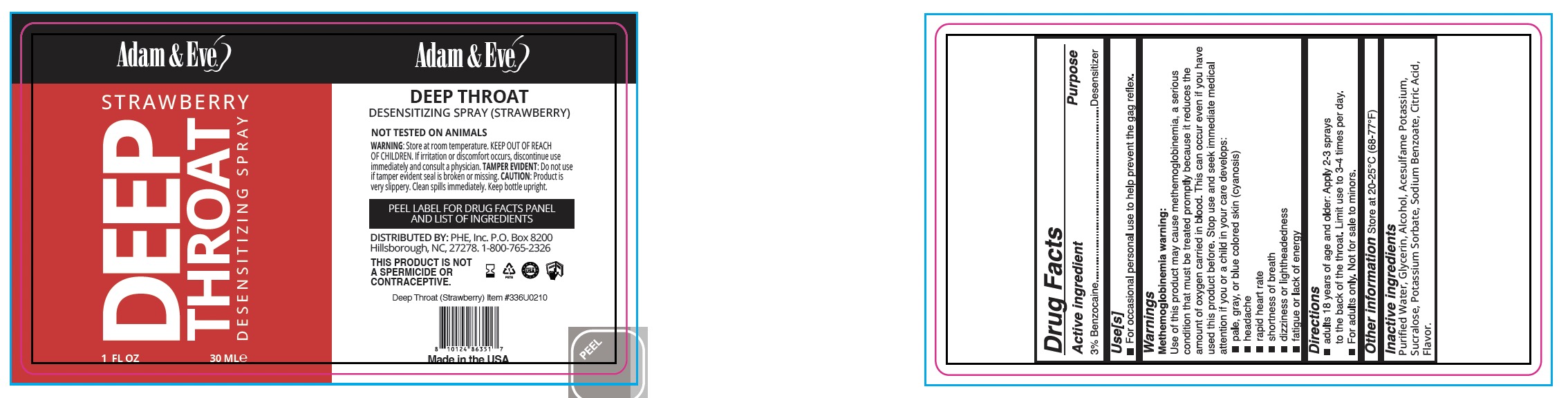 DRUG LABEL: A and E Deep Throat Desensitizing SprayStrawberry
NDC: 87068-183 | Form: SPRAY
Manufacturer: Phe Inc
Category: otc | Type: HUMAN OTC DRUG LABEL
Date: 20251111

ACTIVE INGREDIENTS: BENZOCAINE 3 mg/100 mL
INACTIVE INGREDIENTS: SODIUM BENZOATE; ALCOHOL; ACESULFAME POTASSIUM; GLYCERIN; WATER; SUCRALOSE; CITRIC ACID; POTASSIUM SORBATE

PHE-PLP A&E Deep Throat Desensitizing Spray-strawberry

Active Ingredient(s)

Benzocaine 3%

Purpose

Desensitizer

Use

For occasional personal use to help prevent the gag reflex.

Warnings

Methemoglobinemia warning: Use of this product may cause methemoglobinemia, a serious condition that must be treated promptly because it reduces the amount of oxygen carried in blood. This can occur even if you have used this product before. Stop use and seek immediate medical attention if you or a child in your care develops: ■ pale, gray, or blue colored skin (cyanosis) ■ headache ■ rapid heart rate ■ shortness of breath ■ dizziness or lightheadedness ■ fatigue or lack of energy

KEEP OUT OF REACH OF CHILDREN

Keep out of reach of childeren. Contact a Poison Control Center: This is the emergency contact for accidental overdose or ingestion

Directions

■ adults 18 years of age and older: Apply 2–3 sprays to the back of the throat. Limit use to 3–4 times per day.
■ For adults only. Not for sale to minors.

Other information

Store at 20-25°C (68-77°F)

Inactive ingredients

Purified Water, Glycerin, Alcohol, Acesulfame Potassium, Sucralose, Potassium Sorbate, Sodium Benzoate, Citric Acid, Flavor.